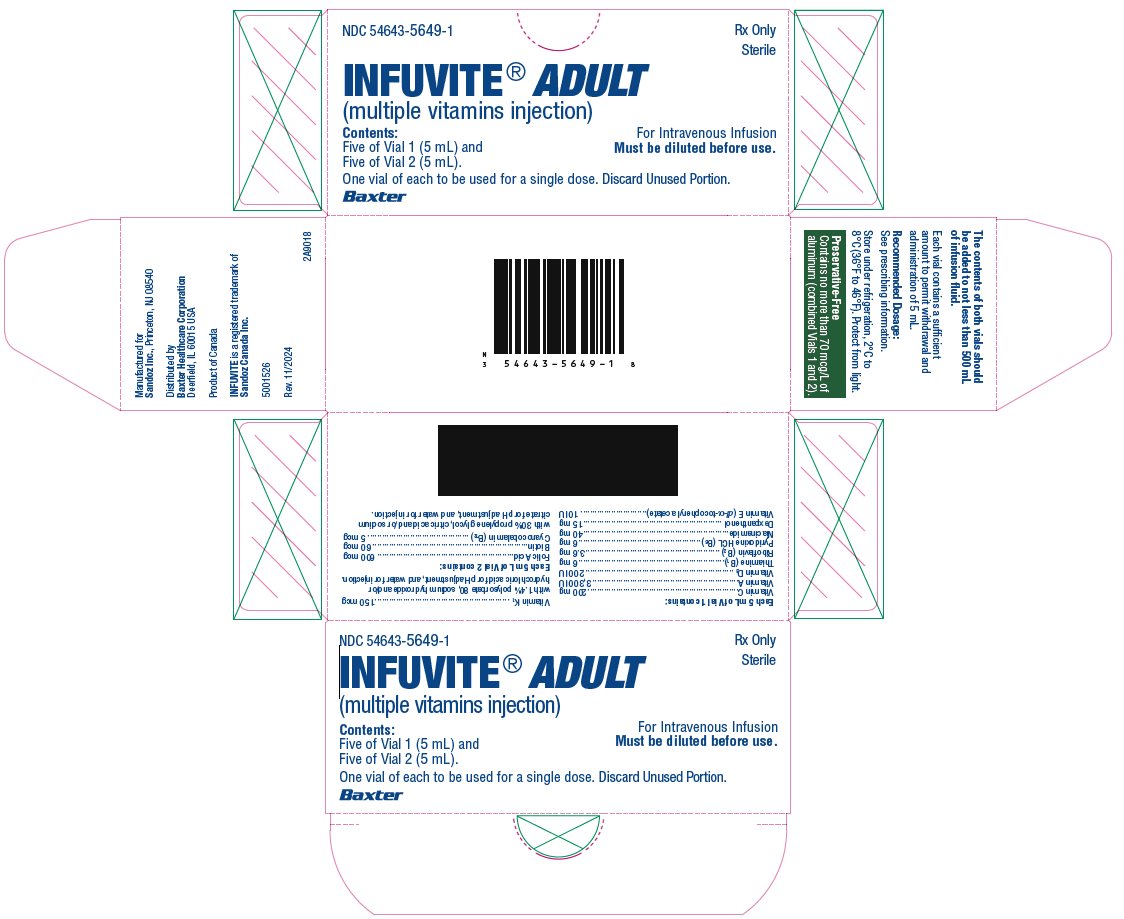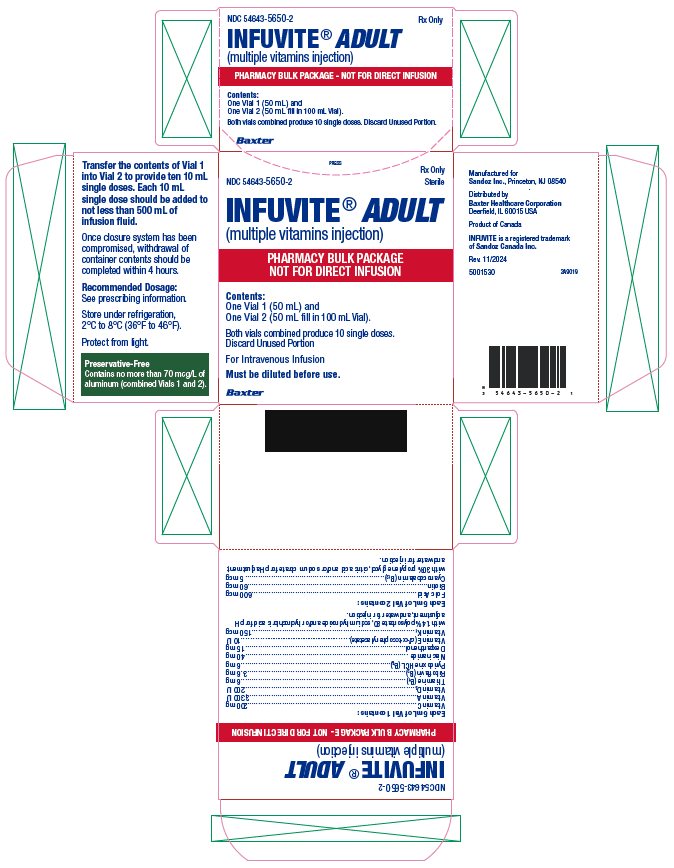 DRUG LABEL: Infuvite Adult
NDC: 54643-5649 | Form: KIT | Route: INTRAVENOUS
Manufacturer: Sandoz Inc
Category: prescription | Type: HUMAN PRESCRIPTION DRUG LABEL
Date: 20241106

ACTIVE INGREDIENTS: ASCORBIC ACID 200 mg/5 mL; VITAMIN A PALMITATE 3300 [iU]/5 mL; CHOLECALCIFEROL 200 [iU]/5 mL; THIAMINE HYDROCHLORIDE 6 mg/5 mL; RIBOFLAVIN 5'-PHOSPHATE SODIUM 3.6 mg/5 mL; PYRIDOXINE HYDROCHLORIDE 6 mg/5 mL; NIACINAMIDE 40 mg/5 mL; DEXPANTHENOL 15 mg/5 mL; PHYTONADIONE 150 ug/5 mL; .ALPHA.-TOCOPHEROL ACETATE, DL- 10 [iU]/5 mL; FOLIC ACID 600 ug/5 mL; BIOTIN 60 ug/5 mL; CYANOCOBALAMIN 5 ug/5 mL
INACTIVE INGREDIENTS: POLYSORBATE 80; SODIUM HYDROXIDE; HYDROCHLORIC ACID; WATER; PROPYLENE GLYCOL; ANHYDROUS CITRIC ACID; SODIUM CITRATE, UNSPECIFIED FORM; WATER

HIGHLIGHTS OF PRESCRIBING INFORMATION

These highlights do not include all the information needed to use INFUVITE ADULT safely and effectively. See full prescribing information for INFUVITE ADULT
INFUVITE ADULT (multiple vitamins injection), for intravenous use
Initial U.S. Approval: 2003

1 INDICATIONS AND USAGE

INFUVITE ADULT is a combination of vitamins indicated for prevention of vitamin deficiency in adults and children aged 11 and older receiving parenteral nutrition (1)

2 DOSAGE AND ADMINISTRATION

- INFUVITE ADULT is a combination product that contains the following vitamins: ascorbic acid, vitamin A, vitamin D, thiamine, riboflavin, pyridoxine, niacinamide, dexpanthenol, vitamin E, vitamin K1, folic acid, biotin, and vitamin B12 (2.1)
- INFUVITE ADULT is for administration by intravenous infusion after dilution (2.1)
- Recommended daily dosage is 10 mL (2.1)
- INFUVITE ADULT is supplied as a single dose and as a pharmacy bulk package.
- Single Dose: Add one daily dose of 10 mL (5 mL from Vial 1 and 5 mL from Vial 2) to not less than 500 mL, and preferably 1000 mL, of intravenous dextrose, saline or similar infusion solutions. (2.2)
- Pharmacy Bulk Package: Add the contents of Vial 1 to the contents of Vial 2. This provides ten 10 mL daily doses. Take 10 mL from Vial 2 and add to not less than 500 mL, and preferably 1000 mL, of intravenous dextrose, saline or similar infusion solutions. (2.2)
- After dilution in an intravenous infusion, refrigerate resulting solution unless used immediately. Use solution within 24 hours after dilution (2.2)
- Monitor blood vitamin concentrations (2.3)
- See Full Prescribing Information for drug incompatibilities (2.4)

3 DOSAGE FORMS AND STRENGTHS

- INFUVITE ADULT supplied as single dose is an injection consisting of two vials labeled Vial 1 (5 mL) and Vial 2 (5 mL) (3)
- INFUVITE ADULT supplied as a pharmacy bulk package is an injection consisting of two vials labeled Vial 1 (50 mL) and Vial 2 (50 mL fill in 100 mL Vial) (3)

4 CONTRAINDICATIONS

- Hypersensitivity to any of the vitamins or excipients (4)
- Existing hypervitaminosis (4)

5 WARNINGS AND PRECAUTIONS

- Risk of Aluminum Toxicity: For at risk patients (renal failure or those with prolonged therapy), consider periodic monitoring of aluminum levels (5.1)
- Allergic Reactions: To thiamine may occur (5.2)
- Hypervitaminosis A: Patients with renal failure or liver disease may be at higher risk (5.3)
- Decreased Anticoagulant Effect of Warfarin: Monitor INR (5.4, 7.1)
- Interferes with Megaloblastic Anemia Diagnosis: Avoid during testing for this disorder (5.5)
- Risk of Vitamin Deficiencies or Excesses: Monitor blood vitamin concentrations (5.6)
- False Negative Urine Glucose Tests: Due to vitamin C (5.7)

6 ADVERSE REACTIONS

Adverse reactions have included anaphylaxis and anaphylactoid reactions including shortness of breath, wheezing and angioedema, rash, erythema, pruritis, headache, dizziness, agitation, anxiety, diplopia (6)

To report SUSPECTED ADVERSE REACTIONS, contact Sandoz Inc. at 1-800-525-8747 or FDA at 1-800-FDA-1088 or www.fda.gov/medwatch.

7 DRUG INTERACTIONS

Effect of INFUVITE ADULT on other drugs:

- Antibiotics: Thiamine, riboflavin, pyridoxine, niacinamide, and ascorbic acid decrease activities of erythromycin, kanamycin, streptomycin, doxycycline, and lincomycin (7.1)
- Bleomycin: Ascorbic acid and riboflavin may reduce the activity of bleomycin (7.1)
- Levodopa: Pyridoxine may decrease blood levels of levodopa and levodopa efficacy may decrease (7.1)
- Phenytoin: Folic acid may decrease phenytoin blood levels and increase risk of seizure activity (7.1)
- Methotrexate: Folic acid may decrease response to methotrexate (7.1)

Effects of other drugs on INFUVITE ADULT:

- Hydralazine, Isoniazid: Concomitant administration of hydralazine or isoniazid may increase pyridoxine requirements (7.2).
- Phenytoin: May decrease folic acid concentrations (7.2)
- Chloramphenicol: In patients with pernicious anemia, the hematologic response to vitamin B12 therapy may be inhibited (7.2)

8 USE IN SPECIFIC POPULATIONS

- Pregnancy and Lactation: Pregnant and lactating patients should follow the U.S. Recommended Daily Allowances for their condition, because their vitamin requirements may exceed those of nonpregnant and nonlactating patients (8.1, 8.2)
- Renal Impairment: Monitor renal function, calcium, phosphorus and vitamin A levels in patients with renal impairment (8.6)
- Hepatic Impairment: Monitor vitamin A level in patients with liver disease, high alcohol consumption (8.7)

FULL PRESCRIBING INFORMATION

1 INDICATIONS AND USAGE

INFUVITE ADULT is a combination of vitamins indicated for the prevention of vitamin deficiency in adults and children aged 11 and older receiving parenteral nutrition.

The physician should not await the development of clinical signs of vitamin deficiency before initiating vitamin therapy.

2 DOSAGE AND ADMINISTRATION

2.1 Important Dosage Instructions

INFUVITE ADULT is a combination product that contains the following vitamins: ascorbic acid, vitamin A, vitamin D, thiamine, riboflavin, pyridoxine, niacinamide, dexpanthenol, vitamin E, vitamin K1, folic acid, biotin, and vitamin B12.

INFUVITE ADULT is supplied as a single dose or as a pharmacy bulk package for intravenous use intended for administration by intravenous infusion after dilution.

INFUVITE ADULT Single Dose:

- Provides one daily dose of 10 mL (5 mL of Vial 1 plus 5 mL of Vial 2) which must be diluted prior to intravenous administration [see Dosage and Administration (2.2)].

INFUVITE ADULT Pharmacy Bulk Package:

- Provides ten 10 mL daily doses when the content of vial 1 is transferred into the content of vial 2. One 10 mL dose is then added directly to intravenous fluid. Pharmacy bulk package of INFUVITE ADULT is intended for dispensing of single doses to multiple patients in a pharmacy admixture program and is restricted to the preparation of admixtures for infusion [see Dosage and Administration (2.2)].

Patients with multiple vitamin deficiencies or with increased vitamin requirements may need multiple daily dosages as indicated. Some patients do not maintain adequate levels of certain vitamins when this formulation in recommended amounts is the only source of vitamins.

2.2 Preparation and Administration Instructions

Do not administer INFUVITE ADULT as a direct, undiluted intravenous injection as it may cause dizziness, faintness, and possible tissue irritation.

INFUVITE ADULT Single Dose:

- Use only in a suitable work area such as a laminar flow hood (or an equivalent clean air compounding area).
- Add 5 mL of Vial 1 and 5 mL of Vial 2 to at least 500 mL to 1000 mL, of intravenous dextrose or saline solutions.
- Discard unused portion.
- Visually inspect for particulate matter and discoloration prior to administration.
- After INFUVITE ADULT is diluted in an intravenous infusion, refrigerate the resulting solution unless it is to be used immediately, and use the solution within 24 hours after dilution.
- Minimize exposure to light because some of the vitamins in INFUVITE ADULT, particularly A, D and riboflavin, are light sensitive.

INFUVITE ADULT Pharmacy Bulk Package:

- Use only in a suitable work area such as a laminar flow hood (or an equivalent clean air compounding area).
- Transfer the contents of Vial 1 into the contents of Vial 2 to provide ten 10 mL single doses.
- Each bulk vial closure shall be penetrated only one time with a suitable sterile transfer device or dispensing set that allows measured dispensing of the contents.
- Once the closure system has been penetrated, complete dispensing from the pharmacy bulk vial should be completed within 4 hours. The mixed solution may be refrigerated and stored for up to 4 hours.
- Discard unused portion.
- Visually inspect for particulate matter and discoloration prior to administration.
- One daily 10 mL dose should be added directly to at least 500 mL to 1000 mL, of intravenous dextrose, saline or similar infusion solutions.
- After INFUVITE ADULT is diluted in an intravenous infusion, refrigerate the resulting solution unless it is to be used immediately, and use the solution within 24 hours after dilution.
- Minimize exposure to light because some of the vitamins in INFUVITE ADULT, particularly A, D and riboflavin, are light sensitive.

2.3 Monitoring Vitamin Blood Levels

Blood vitamin concentrations should be monitored to ensure maintenance of adequate levels, particularly in patients receiving parenteral multivitamins as the only source of vitamins for long periods of time.

2.4 Drug Incompatibilities

- INFUVITE ADULT is not physically compatible with moderately alkaline solutions such as a sodium bicarbonate solution and other alkaline drugs such as acetazolamide sodium, aminophylline, ampicillin sodium, tetracycline HCl and chlorothiazide sodium.
- Folic acid is unstable in the presence of calcium salts such as calcium gluconate.
- Vitamin A and thiamine in INFUVITE ADULT may react with bisulfite solutions such as sodium bisulfite or vitamin K bisulfate.
- Do not add INFUVITE ADULT directly to intravenous fat emulsions.
- Consult appropriate references for additional listings of physical and chemical compatibility of solutions and drugs with the vitamin infusion when needed. If incompatibilities are identified, avoid admixture or Y-site administration with vitamin solutions.

3 DOSAGE FORMS AND STRENGTHS

INFUVITE ADULT Single Dose: is an injection for intravenous administration consisting of two vials labeled Vial 1 (5 mL) and Vial 2 (5 mL). For the vitamin strengths [see Description (11)].

INFUVITE ADULT Pharmacy Bulk Package: is an injection for intravenous administration consisting of two vials labeled Vial 1 (50 mL) and Vial 2 (50 mL Fill in 100 mL Vial). The mixed solution (100 mL) will provide ten 10 mL single doses. For the vitamin strengths [see Description (11)].

Vial 1 (Single Dose and Pharmacy Bulk Package) is supplied as clear, yellow to orange liquid in amber glass vial closed with a rubber stopper, clear aluminum seal and a white flip-off.

Vial 2 (Single Dose and Pharmacy Bulk Package) is supplied as clear, colorless to pale yellow liquid in amber glass vial closed with a rubber stopper, clear aluminum seal and a deep purple flip-off.

4 CONTRAINDICATIONS

INFUVITE ADULT is contraindicated in patients who have

- An existing hypervitaminosis, or
- A history of hypersensitivity due to any vitamins or excipients contained in this formulation.

5 WARNINGS AND PRECAUTIONS

5.1 Aluminum Toxicity

INFUVITE ADULT contains aluminum that may be toxic. Aluminum may reach toxic levels with prolonged parenteral administration if kidney function is impaired. Premature neonates are particularly at risk because their kidneys are immature, and they require large amounts of calcium and phosphate solution, which contain aluminum.

Research indicates that patients with impaired kidney function, including premature neonates who receive parenteral levels of aluminum at greater than 4 to 5 mcg/kg/day accumulate aluminum at levels associated with central nervous system and bone toxicity. Tissue loading may occur at even lower rates of administration. To prevent aluminum toxicity periodically monitor aluminum levels with prolonged parenteral administration of INFUVITE ADULT in patients with renal impairment.

5.2 Allergic Reactions to Thiamine

Allergic reactions such as urticaria, shortness of breath, wheezing and angioedema have been reported following intravenous administration of thiamine, which is found in INFUVITE ADULT. There have been rare reports of anaphylactoid reactions following intravenous doses of thiamine. No fatal anaphylactoid reactions associated with INFUVITE ADULT have been reported.

5.3. Hypervitaminosis A

Hypervitaminosis A, manifested by nausea, vomiting, headache, dizziness, blurred vision has been reported in patients with renal failure receiving 1.5 mg/day retinol and in patients with liver disease, Therefore, supplementation of renal failure patients and patients with liver disease with vitamin A, an ingredient found in INFUVITE ADULT, should be undertaken with caution [see Use in Specific Populations (8.6 and 8.7)].

5.4 Decreased Anticoagulant Effect of Warfarin

INFUVITE ADULT contains Vitamin K, which may decrease the anticoagulant action of warfarin. In patients who are on warfarin anticoagulant therapy receiving INFUVITE ADULT monitor blood levels of prothrombin/INR to determine if dose of warfarin needs to be adjusted.

5.5 Interference with Diagnosis of Megaloblastic Anemia

INFUVITE ADULT contains folic acid and cyanocobalamin which can mask serum deficiencies of folic acid and cyanocobalamin in patients with megaloblastic anemia. Avoid the use of INFUVITE ADULT in patients with suspected or diagnosed megaloblastic anemia prior to blood sampling for the detection of the folic acid and cyanocobalamin deficiencies.

5.6 Potential to Develop Vitamin Deficiencies or Excesses

In patients receiving parenteral multivitamins such as with INFUVITE ADULT, blood concentration should be periodically monitored to determine if deficiencies or excesses are developing. INFUVITE ADULT may not correct long-standing specific vitamin deficiencies. The administration of additional therapeutic doses of specific vitamins may be required [see Dosage and Administration (2.3)].

5.7 Interference with Urine Glucose Testing

INFUVITE ADULT contains vitamin C which is also known as ascorbic acid. Ascorbic acid in the urine may cause false negative urine glucose results.

6 ADVERSE REACTIONS

The following adverse reactions are discussed in greater detail in other section of the labeling.

- Allergic reactions to thiamine [see Warnings and Precautions (5.2)]
- Hypervitaminosis A [see Warnings and Precautions (5.3)]

The following adverse reactions have been identified during postapproval use of INFUVITE ADULT. Because these reactions are reported voluntarily from a population of uncertain size, it is not always possible to reliably estimate their frequency or establish a causal relationship to drug exposure.

Dermatologic: rash, erythema, pruritis

CNS: headache, dizziness, agitation, anxiety

Ophthalmic: diplopia

7 DRUG INTERACTIONS

A number of interactions between vitamins and drugs have been reported. The following are examples of these types of interactions:

7.1 Drug Interactions Affecting Co-Administered Drugs

Warfarin: Vitamin K, a component of INFUVITE ADULT, antagonizes the anticoagulant action of warfarin. In patients who are co-administered warfarin and INFUVITE ADULT, blood levels of prothrombin/INR should be monitored to determine if dose of warfarin needs to be adjusted [see Warnings and Precautions (5.4)].

Antibiotics: Thiamine, riboflavin, pyridoxine, niacinamide, and ascorbic acid decrease antibiotic activities of erythromycin, kanamycin, streptomycin, doxycycline, and lincomycin.

Bleomycin: Ascorbic acid and riboflavin inactivate bleomycin in vitro, thus the activity of bleomycin may be reduced.

Levodopa: Pyridoxine may increase the metabolism of levodopa (decrease blood levels of levodopa) and decrease its efficacy.

Phenytoin: Folic acid may increase phenytoin metabolism and lower the serum concentration of phenytoin resulting in increased seizure activity.

Methotrexate: Folic acid may decrease a patient’s response to methotrexate therapy.

7.2 Drug Interactions Affecting Vitamin Levels

Hydralazine, Isoniazid: Concomitant administration of hydralazine or isoniazid may increase pyridoxine requirements.

Phenytoin: Phenytoin may decrease serum folic acid concentrations.

Chloramphenicol: In patients with pernicious anemia, the hematologic response to vitamin B12 therapy may be inhibited by chloramphenicol.

8 USE IN SPECIFIC POPULATIONS

8.1 Pregnancy

Risk Summary

Administration of the approved recommended dose of INFUVITE ADULT in parental nutrition is not expected to cause major birth defects, miscarriage, or adverse maternal or fetal outcomes. Pregnant patients should follow the U.S. Recommended Daily Allowances for pregnancy because their vitamin requirements may exceed those of nonpregnant patients. Deficiency of essential vitamins may result in adverse pregnancy outcomes (see Clinical Considerations). Animal reproduction studies have not been conducted with INFUVITE ADULT.

The estimated background risk of major birth defects and miscarriage for the indicated population is unknown. All pregnancies have a background risk of birth defect, loss, or other adverse outcomes. In the U.S. general population, the estimated background risk of major birth defects and miscarriage in clinically recognized pregnancies is 2-4% and 15-20%, respectively.

Clinical Considerations

Disease-associated Maternal and/or Embryo-Fetal Risk

Deficiency of essential vitamins has been associated with adverse pregnancy and fetal outcomes, such as maternal folic acid deficiency and an increased risk of neural tube defects. Therefore, parenteral nutrition with multiple vitamins injection should be considered if a pregnant woman’s nutritional requirements cannot be fulfilled by oral or enteral intake.

8.2 Lactation

Risk Summary

Multiple vitamins present in INFUVITE ADULT are also present in human milk. Administration of the approved recommended dose of INFUVITE ADULT In parental nutrition is not expected to cause harm to a breastfed infant. There is no information on the effects of INFUVITE ADULT on milk production. Lactating patients should follow the U.S. Recommended Daily Allowances for their condition, because their vitamin requirements may exceed those of nonlactating patients. The developmental and health benefits of breastfeeding should be considered along with the mother’s clinical need for INFUVITE ADULT and any potential adverse effects on the breastfed child from INFUVITE ADULT or from the underlying maternal condition.

8.4 Pediatric Use

Safety and effectiveness in children below the age of 11 years have not been established.

8.5 Geriatric Use

Safety and effectiveness for geriatric use have not been established.

8.6 Renal Impairment

INFUVITE ADULT has not been studied in patients with renal impairment. Monitor renal function, calcium, phosphorus and vitamin A levels in patients with renal impairment [see Warnings and Precautions (5.1 and 5.3)].

8.7 Hepatic Impairment

INFUVITE ADULT has not been studied in patients with liver impairments. Monitor vitamin A level in patients with liver disease, high alcohol consumption [see Warnings and Precautions (5.3)].

10 OVERDOSAGE

Signs and symptoms of acute or chronic overdosage may be those of individual INFUVITE ADULT component toxicity. In post-marketed surveillance, overdosage with INFUVITE ADULT at two times the prescribed dose did not result in toxicity.

11 DESCRIPTION

INFUVITE ADULT (multiple vitamins injection) is a sterile product consisting of two vials provided as a single dose or as a pharmacy bulk package, both intended for intravenous use for administration by intravenous infusion after dilution:

INFUVITE ADULT Single Dose- two 5 mL single-dose vials labeled Vial 1 and Vial 2.

INFUVITE ADULT Pharmacy Bulk Package- two vials – 1 each of Vial 1 (50 mL) and Vial 2 (50 mL Fill in 100 mL Vial). The mixed solution (100 mL) will provide ten 10 mL single doses.

Each 5 mL of Vial 1 contains:

Ascorbic acid (Vitamin C) | 200 mg
Vitamin A* (as palmitate) | 3,300 IU
Vitamin D3* (cholecalciferol) | 200 IU
Thiamine (Vitamin B1) (as the hydrochloride) | 6 mg
Riboflavin (Vitamin B2) (as riboflavin 5-phosphate sodium) | 3.6 mg
Pyridoxine HCl (Vitamin B6) | 6 mg
Niacinamide | 40 mg
Dexpanthenol (as d-pantothenyl alcohol) | 15 mg
Vitamin E* (dl-α-tocopheryl acetate) | 10 IU
Vitamin K1* | 150 mcg

*Polysorbate 80 is used to water solubilize the oil-soluble vitamins A, D, E, and K.

Inactive ingredients: 1.4% polysorbate 80, sodium hydroxide and/or hydrochloric acid for pH adjustment, and water for injection.

Each 5 mL of Vial 2 contains:

Folic acid | 600 mcg
Biotin | 60 mcg
Vitamin B12 (cyanocobalamin) | 5 mcg

Inactive ingredients: 30% propylene glycol, citric acid and/or sodium citrate for pH adjustment, and water for injection.

INFUVITE ADULT makes available a combination of important oil-soluble and water-soluble vitamins in an aqueous solution, formulated for incorporation into intravenous solutions. The liposoluble vitamins A, D, E, and K have been solubilized in an aqueous medium with polysorbate 80, permitting intravenous administration of these vitamins.

Contains no more than 70 mcg/L of aluminum (combined Vials 1 and 2).

13 NONCLINICAL TOXICOLOGY

13.1 Carcinogenesis, Mutagenesis, Impairment of Fertility

Carcinogenicity, mutagenicity, and fertility studies have not been performed with INFUVITE ADULT.

16 HOW SUPPLIED/STORAGE AND HANDLING

How Supplied

INFUVITE ADULT (multiple vitamins injection) is supplied as follows:

Vial 1 (Single Dose and Pharmacy Bulk Package) is supplied as clear, yellow to orange liquid in amber glass vial closed with a rubber stopper, clear aluminum seal and a white flip-off.

Vial 2 (Single Dose and Pharmacy Bulk Package) is supplied as clear, colorless to pale yellow liquid in amber glass vial closed with a rubber stopper, clear aluminum seal and a deep purple flip-off.

INFUVITE ADULT Single Dose:

Carton contains total ten single-dose vials | NDC 54643-5649-1
Five of Vial 1 (5 mL) | NDC 54643-5657-1
Five of Vial 2 (5 mL) | NDC 54643-5659-1

one Vial 1 plus one Vial 2 to be used for a single dose [see Dosage and Administration (2.1)].

INFUVITE ADULT Pharmacy Bulk Package:

Carton contains total two vials | NDC 54643-5650-2
One Vial 1 (50 mL) | NDC 54643-5661-2
One Vial 2 (50 mL Fill in 100 mL Vial) | NDC 54643-5663-2

Mix contents of Vial 1 with Vial 2 to provide 10 single doses [see Dosage and Administration (2.1)].

Storage and Handling

Minimize exposure of INFUVITE ADULT to light because vitamins A, D and riboflavin are light sensitive.

Store under refrigeration, 2°C to 8°C (36°F to 46°F).

17 PATIENT COUNSELING INFORMATION

Instruct patients (if age appropriate) and caregivers:

- To watch for signs of allergic reactions such as urticaria, shortness of breath, wheezing and angioedema since hypersensitivity reactions may occur to any of the vitamins or excipients contained in INFUVITE ADULT.
- To watch for and immediately report nausea, vomiting, headache, dizziness, blurred vision, especially if patients have renal impairment, as these may be signs of hypervitaminosis A.
- To report other adverse reactions such as rash, erythema, pruritus, headache, dizziness, agitation, anxiety, and diplopia.
- That the patients on warfarin anticoagulant therapy will be monitored periodically with blood prothrombin/ INR levels to determine if their dose of warfarin needs to be adjusted.
- About the significance of periodic monitoring of blood vitamin concentrations to determine if vitamin deficiencies or excesses are developing and the need to monitor renal function, calcium, phosphorus, aluminum and vitamin A levels in patients with renal impairment.
- That INFUVITE ADULT should be avoided in patients with suspected or diagnosed megaloblastic anemia prior to blood sampling for the detection of the folic acid and cyanocobalamin deficiencies.
- That vitamin C (ascorbic acid) contained in INFUVITE ADULT may cause false negative urine glucose results.

Manufactured for

Sandoz Inc., Princeton, NJ 08540

Distributed by

Baxter Healthcare Corporation

Deerfield, IL 60015 USA

INFUVITE is a registered trademark of Sandoz Canada Inc.

5001527

Infuvite Adult Single Dose Vials Carton

NDC 54643-5649-1 Rx Only Sterile

INFUVITE® ADULT (multiple vitamins injection)

Contents:

Five of Vial 1 (5 mL) and

Five of Vial 2 (5 mL).

One vial of each to be used for a single dose. Discard Unused Portion.

For Intravenous Infusion

Must be diluted before use.

Baxter

Infuvite Adult Pharmacy Bulk Vials Carton

NDC 54643-5650-2 Rx Only Sterile

INFUVITE® ADULT (multiple vitamins injection)

PHARMACY BULK PACKAGE

NOT FOR DIRECT INFUSION

Contents:

One Vial 1 (50 mL) and

One Vial 2 (50 mL fill in 100 mL Vial).

Both vials combined produce 10 single doses. Discard Unused Portion

For Intravenous Infusion

Must be diluted before use.

Baxter